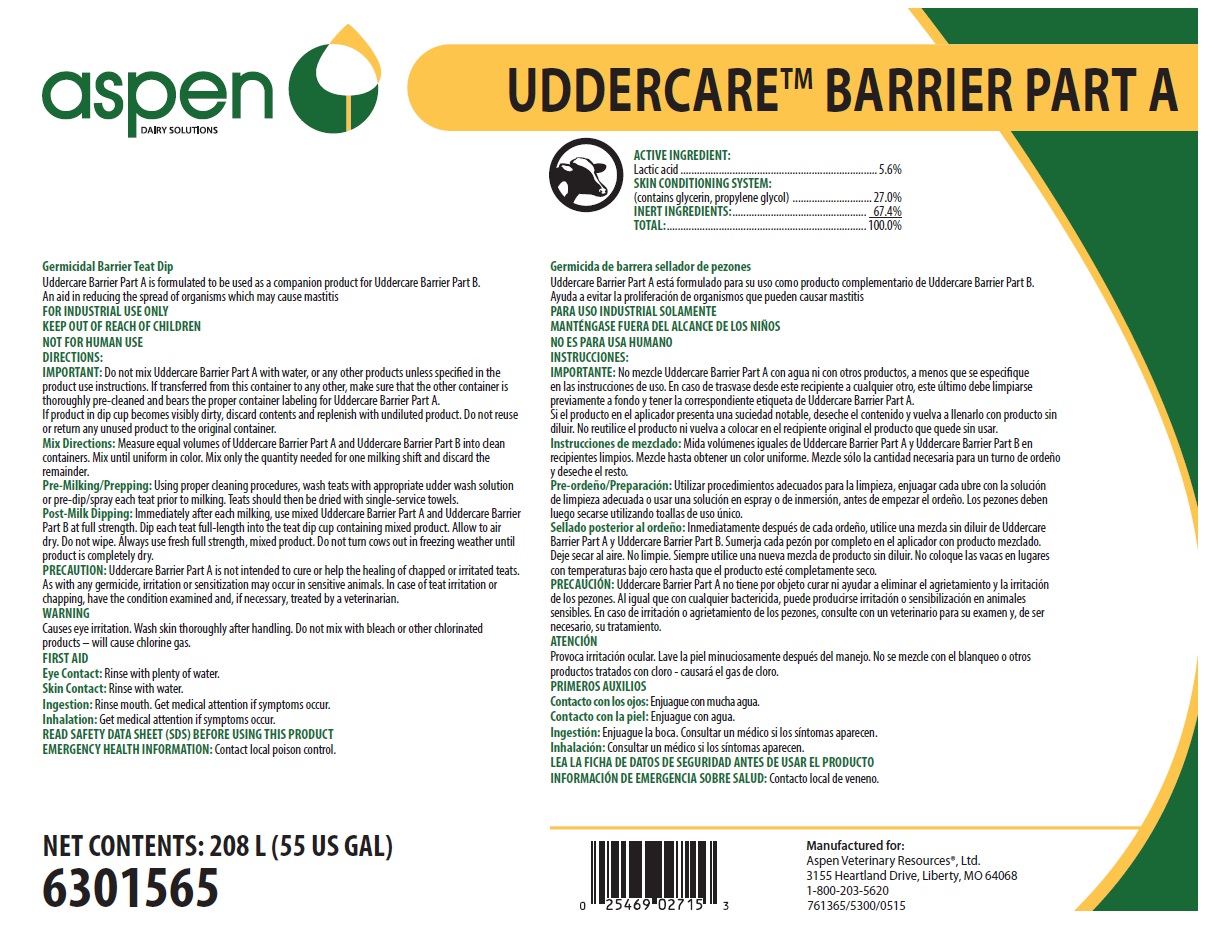 DRUG LABEL: Uddercare Barrier Part A
NDC: 46066-415 | Form: SOLUTION
Manufacturer: Aspen Veterinary Resources
Category: animal | Type: OTC ANIMAL DRUG LABEL
Date: 20250714

ACTIVE INGREDIENTS: LACTIC ACID 56 mg/1 mL
INACTIVE INGREDIENTS: WATER; GLYCERIN; PROPYLENE GLYCOL

SAFE HANDLING WARNING

FOR INDUSTRIAL USE ONLY

KEEP OUT OF REACH OF CHILDREN

NOT FOR HUMAN USE

WARNING

Causes eye irritation. Wash skin thoroughly after handling. Do not mix with bleach or other chlorinated products – will cause chlorine gas.

DIRECTIONS:

IMPORTANT: Do not mix Uddercare Barrier Part A with water, or any other products unless specified in the product use instructions. If transferred from this container to any other, make sure that the other container is thoroughly pre-cleaned and bears the proper container labeling for Uddercare Barrier Part A.

If product in dip cup becomes visibly dirty, discard contents and replenish with undiluted product. Do not reuse or return any unused product to the original container.

Mix Directions: Measure equal volumes of Uddercare Barrier Part A and Uddercare Barrier Part B into clean containers. Mix until uniform in color. Mix only the quantity needed for one milking shift and discard the remainder.

Pre-Milking/Prepping: Using proper cleaning procedures, wash teats with appropriate udder wash solution or pre-dip/spray each teat prior to milking. Teats should then be dried with single-service towels.

Post-Milk Dipping: Immediately after each milking, use mixed Uddercare Barrier Part A and Uddercare Barrier Part B at full strength. Dip each teat full-length into the teat dip cup containing mixed product. Allow to air dry. Do not wipe. Always use fresh full strength, mixed product. Do not turn cows out in freezing weather until product is completely dry.

PRECAUTION: Uddercare Barrier Part A is not intended to cure or help the healing of chapped or irritated teats. As with any germicide, irritation or sensitization may occur in sensitive animals. In case of teat irritation or chapping, have the condition examined and, if necessary, treated by a veterinarian.

OTHER SAFETY INFORMATION

FIRST AID

Eye Contact: Rinse with plenty of water.

Skin Contact: Rinse with water.

Ingestion: Rinse mouth. Get medical attention if symptoms occur.

Inhalation: Get medical attention if symptoms occur.

READ SAFETY DATA SHEET (SDS) BEFORE USING THIS PRODUCT

EMERGENCY HEALTH INFORMATION: Contact local poison control.

PACKAGE LABEL

aspen DAIRY SOLUTIONS
UDDERCARE BARRIER PART A

Germicidal Barrier Teat Dip
Uddercare Barrier Part A is formulated to be used as a companion product for Uddercare Barrier Part B.
An aid in reducing the spread of organisms which may cause mastitis

ACTIVE INGREDIENT:
Lactic acid......................................................................... 5.6%
SKIN CONDITIONING SYSTEM:
(contains glycerin, propylene glycol) .............................. 27.0%
INERT INGREDIENTS:.................................................. 67.4%
TOTAL:.......................................................................... 100.0%

NET CONTENTS: 208 L (55 US GAL)
6301565

Manufactured for:
Aspen Veterinary Resources®, Ltd.
3155 Heartland Drive, Liberty, MO 64068
1-800-203-5620
761365/5300/0515